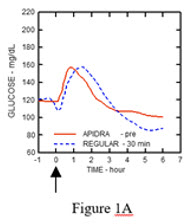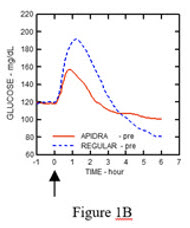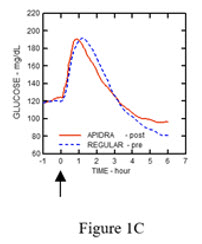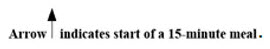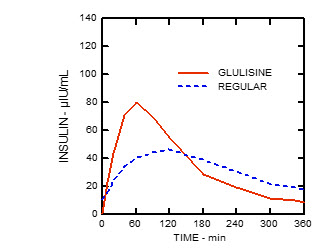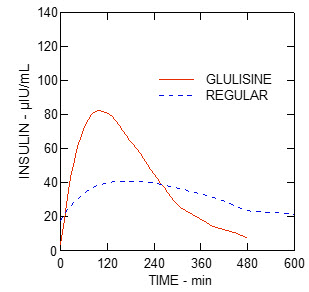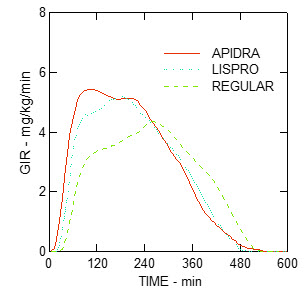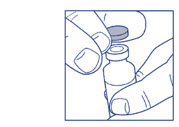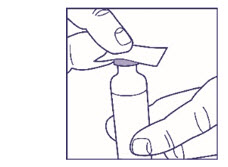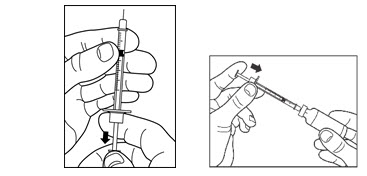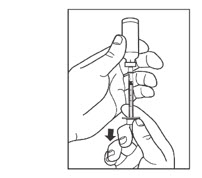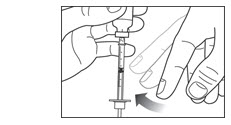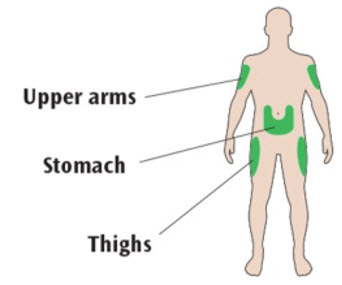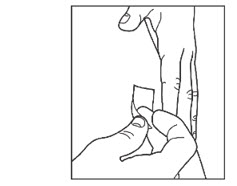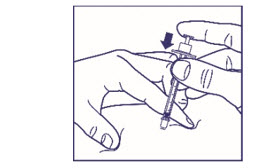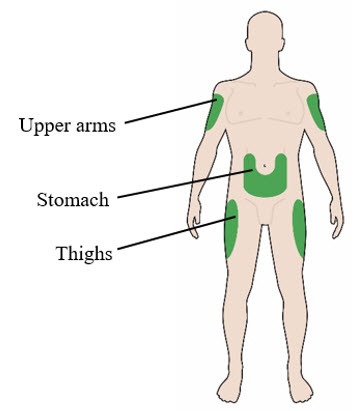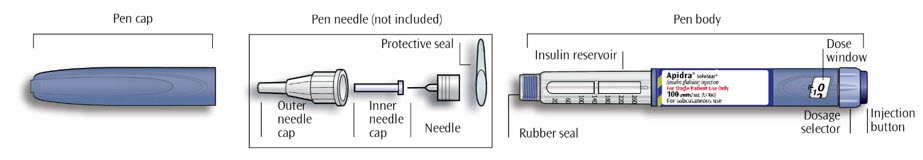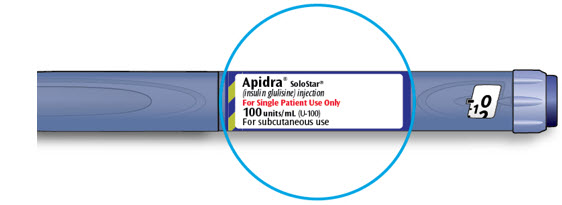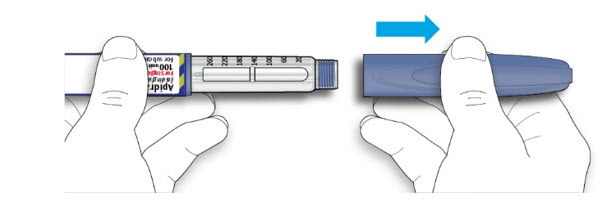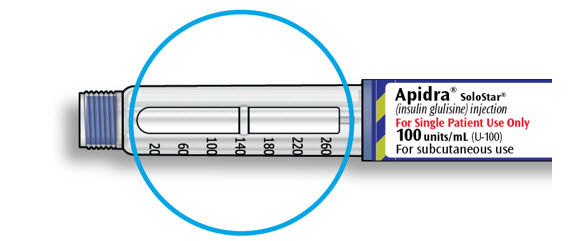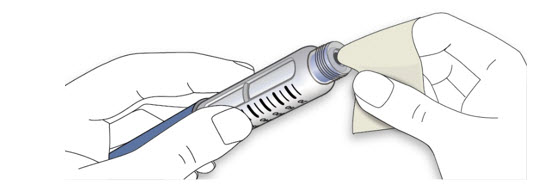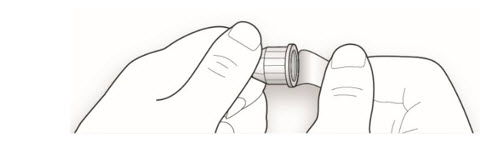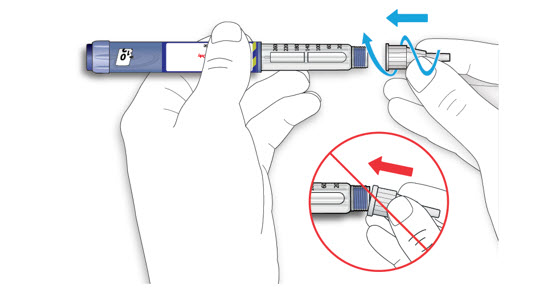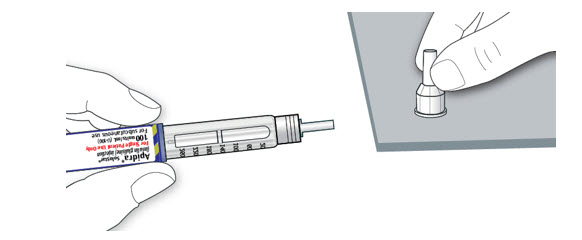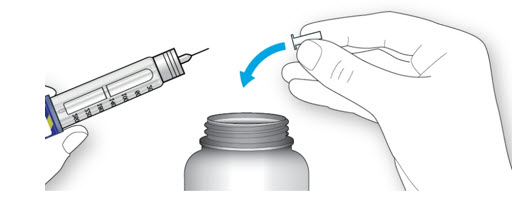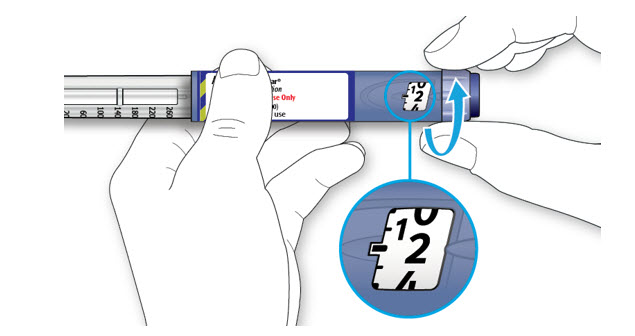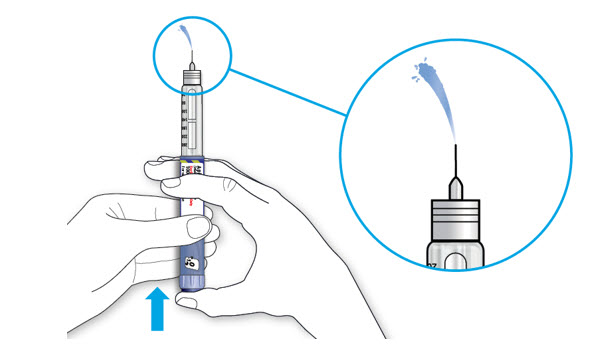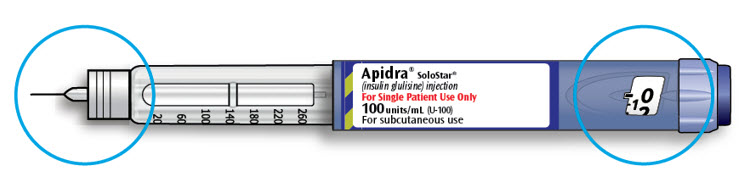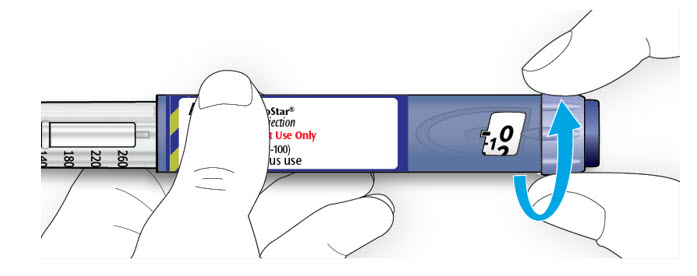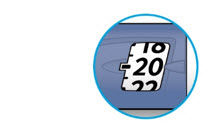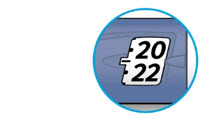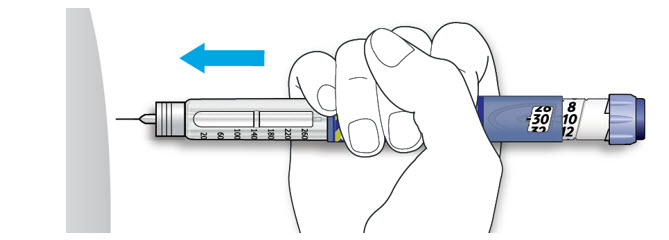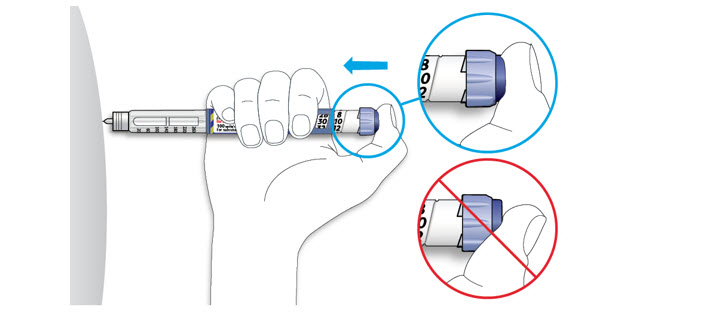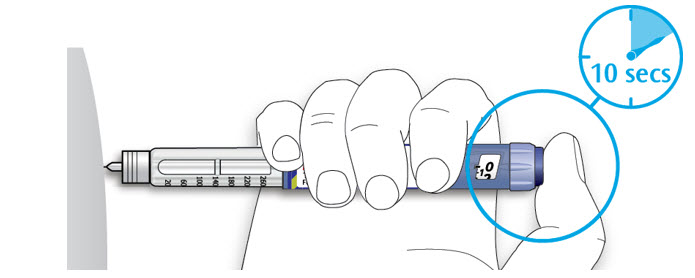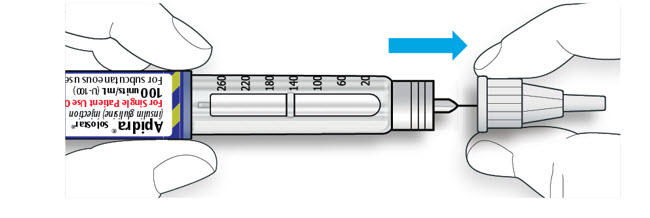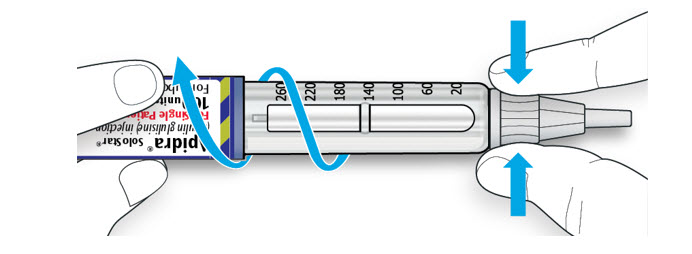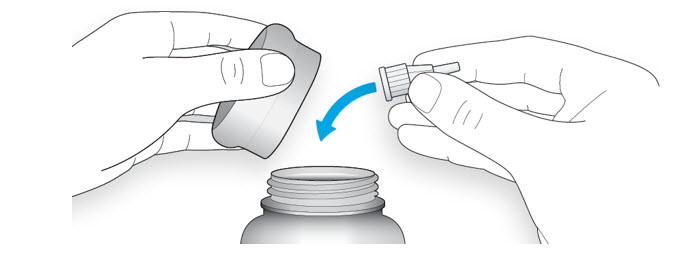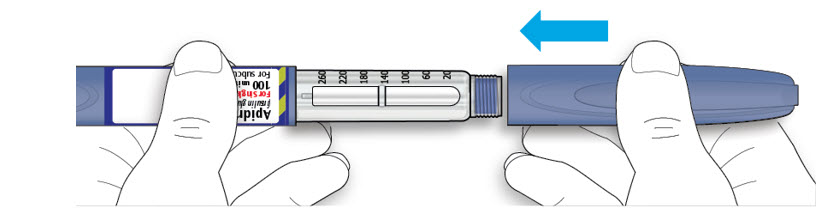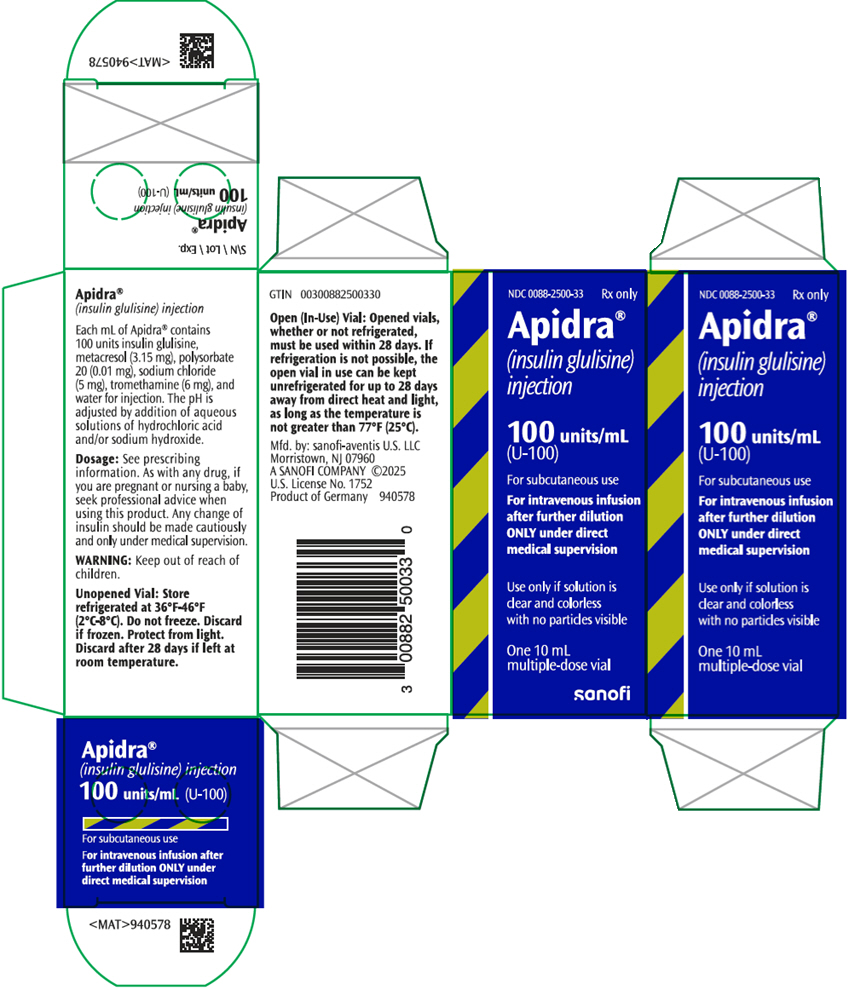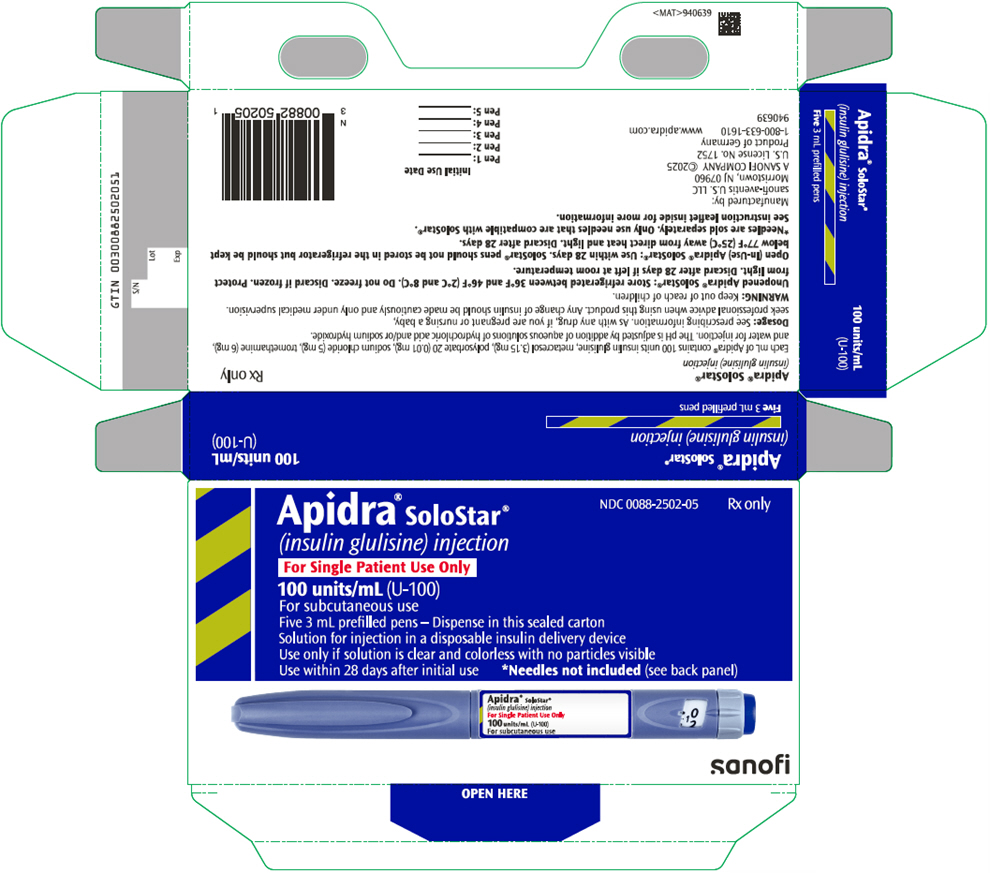 DRUG LABEL: Apidra
NDC: 0088-2500 | Form: INJECTION, SOLUTION
Manufacturer: sanofi-aventis U.S. LLC
Category: prescription | Type: HUMAN PRESCRIPTION DRUG LABEL
Date: 20251125

ACTIVE INGREDIENTS: INSULIN GLULISINE 100 [iU]/1 mL
INACTIVE INGREDIENTS: METACRESOL 3.15 mg/1 mL; TROMETHAMINE 6 mg/1 mL; SODIUM CHLORIDE 5 mg/1 mL; POLYSORBATE 20 0.01 mg/1 mL; WATER; HYDROCHLORIC ACID; SODIUM HYDROXIDE

HIGHLIGHTS OF PRESCRIBING INFORMATION

These highlights do not include all the information needed to use APIDRA safely and effectively. See full prescribing information for APIDRA.
APIDRA® (insulin glulisine) injection, for subcutaneous or intravenous use
Initial U.S. Approval: 2004

1 INDICATIONS AND USAGE

APIDRA is a rapid-acting human insulin analog indicated to improve glycemic control in adult and pediatric patients with diabetes mellitus. (1)

2 DOSAGE AND ADMINISTRATION

- See Full Prescribing Information for important administration instructions. (2.1, 2.2)
- Individualize and adjust the dosage of APIDRA based on route of administration, individual's metabolic needs, blood glucose monitoring results, and glycemic control goal. (2.3)
- Dosage adjustments may be needed when switching from another insulin, with changes in physical activity, changes in concomitant medications, changes in meal patterns, changes in renal or hepatic function or during acute illness. (2.3)
- Subcutaneous Injection: (2.2)
  - Inject within 15 minutes before a meal or within 20 minutes after starting a meal into the abdomen, thigh, or upper arm.
  - Rotate injection sites within the same region to reduce the risk of lipodystrophy and localized cutaneous amyloidosis.
  - Should generally be used in regimens with an intermediate or long-acting insulin.
- Continuous Subcutaneous Infusion (Insulin Pump): (2.2)
  - Refer to the insulin infusion pump user manual to see if APIDRA can be used. Use in accordance with the insulin pump instructions for use.
  - Administer by continuous subcutaneous infusion using an insulin pump in a region recommended in the instructions from the pump manufacturer.
  - Rotate infusion sites within the same region to reduce the risk of lipodystrophy and localized cutaneous amyloidosis.
  - Do not mix with other insulins or diluents in the pump.

- Intravenous Administration: Administer only under medical supervision after diluting to concentrations from 0.05 to 1 unit/mL APIDRA in 0.9% sodium chloride injection, USP using polyvinyl chloride infusion bags. (2.2)

3 DOSAGE FORMS AND STRENGTHS

Injection 100 units/mL (U-100) is available as: (3)

- 10 mL multiple-dose vial
- 3 mL single-patient-use SoloStar® prefilled pen

4 CONTRAINDICATIONS

- Do not use during episodes of hypoglycemia. (4)
- Do not use in patients with hypersensitivity to insulin glulisine or any excipients in APIDRA (4)

5 WARNINGS AND PRECAUTIONS

- Never share an APIDRA SoloStar pen between patients, even if the needle is changed. (5.1)
- Hyperglycemia or Hypoglycemia with Changes in Insulin Regimen: Make changes to a patient's insulin regimen (e.g., insulin strength, manufacturer, type, injection site or method of administration) under close medical supervision with increased frequency of blood glucose monitoring. (5.2)
- Hypoglycemia: May be life-threatening. Increase frequency of glucose monitoring with changes to: insulin dosage, coadministered glucose lowering medications, meal pattern, physical activity; and in patients with renal impairment or hepatic impairment or hypoglycemia unawareness. (5.3)
- Hypoglycemia Due to Medication Errors: Accidental mix-ups between insulin products can occur. Instruct patients to check insulin labels before injection. (5.4)
- Hypokalemia: May be life-threatening. Monitor potassium levels in patients at risk for hypokalemia and treat if indicated. (5.5)
- Hypersensitivity Reactions: Severe, life-threatening, generalized allergy, including anaphylaxis, can occur. Discontinue APIDRA, monitor and treat if indicated. (5.6)
- Fluid Retention and Heart Failure Can Occur with Concomitant Use of Thiazolidinediones (TZDs): Observe for signs and symptoms of heart failure; consider dosage reduction or discontinuation of TZD if heart failure occurs. (5.7)
- Hyperglycemia and Ketoacidosis Due to Insulin Pump Device Malfunction: Monitor glucose and administer APIDRA by subcutaneous injection if pump malfunction occurs. (5.8)

6 ADVERSE REACTIONS

Adverse reactions commonly associated with APIDRA include hypoglycemia, allergic reactions, injection site reactions, lipodystrophy, pruritus, rash, and weight gain. (6.1)

To report SUSPECTED ADVERSE REACTIONS, contact sanofi-aventis at 1-800-633-1610 or FDA at 1-800-FDA-1088 or www.fda.gov/medwatch.

7 DRUG INTERACTIONS

- Drugs that Affect Glucose Metabolism: Adjustment of insulin dosage may be needed. (7)
- Antiadrenergic Drugs (e.g., beta-blockers, clonidine, guanethidine, and reserpine): Signs and symptoms of hypoglycemia may be reduced or absent. (5.3, 7)

FULL PRESCRIBING INFORMATION

1 INDICATIONS AND USAGE

APIDRA is indicated to improve glycemic control in adult and pediatric patients with diabetes mellitus.

2 DOSAGE AND ADMINISTRATION

2.1 Important Administration Instructions

- Always check insulin label before administration [see Warnings and Precautions (5.4)].
- Inspect visually for particulate matter and discoloration. Only use APIDRA if the solution appears clear and colorless.
- Use APIDRA SoloStar prefilled pen with caution in patients with visual impairment who may rely on audible clicks to dial their dose.

2.2 Route of Administration Instructions

Subcutaneous Injection

- Inject APIDRA subcutaneously within 15 minutes before a meal or within 20 minutes after starting a meal into the abdominal wall, thigh, or upper arm.
- Rotate injection sites within the same region from one injection to the next to reduce the risk of lipodystrophy and localized cutaneous amyloidosis. Do not inject into areas of lipodystrophy or localized cutaneous amyloidosis [see Warnings and Precautions (5.2), Adverse Reactions (6)].
- APIDRA given by subcutaneous injection should generally be used in regimens with an intermediate or long-acting insulin.
- The APIDRA SoloStar prefilled pen dials in 1-unit increments.
- Do not mix APIDRA for subcutaneous injection with insulins other than NPH insulin. If APIDRA is mixed with NPH insulin, draw APIDRA into the syringe first and inject immediately after mixing.

Continuous Subcutaneous Infusion (Insulin Pump)

- Refer to the continuous subcutaneous insulin infusion pump user manual to see if APIDRA can be used with the insulin pump. Use APIDRA in accordance with the insulin pump system's instructions for use.
- Administer APIDRA by continuous subcutaneous infusion in a region recommended in the instructions from the pump manufacturer. Rotate infusion sites within the same region to reduce the risk of lipodystrophy and localized cutaneous amyloidosis. [see Warnings and Precautions (5.2), Adverse Reactions (6)].
- Train patients using continuous subcutaneous insulin infusion pump therapy to administer insulin by injection and have alternate insulin therapy available in case of insulin pump failure [see Warnings and Precautions (5.8)].
- During changes to a patient's insulin regimen, increase the frequency of blood glucose monitoring [see Warnings and Precautions (5.2)].
- Change APIDRA in the reservoir at least every 48 hours or according to the pump user manual, whichever is shorter.
- Change the infusion sets and the infusion set insertion site according to the manufacturer's user manual.
- Do not dilute or mix APIDRA when administering by continuous subcutaneous infusion.
- Do not expose APIDRA in the pump reservoir to temperatures greater than 98.6°F (37°C).

Intravenous Administration

- Administer APIDRA intravenously only under medical supervision with close monitoring of blood glucose and potassium levels to avoid hypoglycemia and hypokalemia [see Warnings and Precautions (5.3, 5.5)].
- Dilute APIDRA to concentrations from 0.05 unit/mL to 1 unit/mL insulin glulisine in infusion systems using polyvinyl chloride (PVC) infusion bags.
- Diluted APIDRA is stable at room temperature for 48 hours only in normal saline solution (0.9% Sodium Chloride Injection, USP) [see How Supplied/Storage and Handling (16.2)].
- APIDRA is not compatible with Dextrose solution and Ringers solution.

2.3 Dosage Information

- Individualize and adjust the dosage of APIDRA based on the patient's metabolic needs, blood glucose monitoring results, and glycemic control goal.
- Dose adjustments may be needed when switching from another insulin, with changes in physical activity, changes in concomitant medications, changes in meal patterns (i.e., macronutrient content or timing of food intake), changes in renal or hepatic function, or during acute illness to minimize the risk of hypoglycemia or hyperglycemia [see Warnings and Precautions (5.2, 5.3), Drug Interactions (7), Use in Specific Populations (8.6, 8.7)].

3 DOSAGE FORMS AND STRENGTHS

Injection: 100 units per mL (U-100), a clear and colorless solution available as:

- 10 mL multiple-dose vial
- 3 mL single-patient-use APIDRA SoloStar prefilled pen

4 CONTRAINDICATIONS

APIDRA is contraindicated:

- during episodes of hypoglycemia
- in patients with known hypersensitivity to insulin glulisine or to any of the excipients in APIDRA; systemic allergic reactions have occurred with APIDRA [see Adverse Reactions (6.1)].

5 WARNINGS AND PRECAUTIONS

5.1 Never Share an APIDRA SoloStar Pen or Syringe or Needle between Patients

APIDRA SoloStar pens must never be shared between patients, even if the needle is changed. Patients using APIDRA vials must never reuse or share needles or syringes with another person. Sharing poses a risk for transmission of blood-borne pathogens.

5.2 Hyperglycemia or Hypoglycemia with Changes in Insulin Regimen

Changes in an insulin regimen (e.g., insulin, insulin strength, manufacturer, type, injection site or method of administration) may affect glycemic control and predispose to hypoglycemia [see Warnings and Precautions (5.3)] or hyperglycemia. Repeated insulin injections into areas of lipodystrophy or localized cutaneous amyloidosis have been reported to result in hyperglycemia; a sudden change in the injection site (to unaffected area) has been reported to result in hypoglycemia [see Adverse Reactions (6)].

Make any changes to a patient's insulin regimen under close medical supervision with increased frequency of blood glucose monitoring. Advise patients who have repeatedly injected into areas of lipodystrophy or localized cutaneous amyloidosis to change the injection site to unaffected areas and closely monitor for hypoglycemia. For patients with type 2 diabetes, dosage adjustments in concomitant oral antidiabetic treatment may be needed.

5.3 Hypoglycemia

Hypoglycemia is the most common adverse reaction of all insulins, including APIDRA [see Adverse Reactions (6.1)]. Severe hypoglycemia can cause seizures, may lead to unconsciousness, may be life-threatening, or cause death. Hypoglycemia can impair concentration ability and reaction time; this may place the patient and others at risk in situations where these abilities are important (e.g., driving or operating other machinery). APIDRA, or any insulin, should not be used during episodes of hypoglycemia [see Contraindications (4)].

Hypoglycemia can happen suddenly, and symptoms may differ in each patient and change over time in the same patient. Symptomatic awareness of hypoglycemia may be less pronounced in patients with longstanding diabetes, in patients with diabetic neuropathy, in patients using medications that block the sympathetic nervous system (e.g., beta-blockers) [see Drug Interactions (7)], or in patients who experience recurrent hypoglycemia.

Risk Factors for Hypoglycemia

The risk of hypoglycemia after an injection is related to the duration of action of the insulin and, in general, is highest when the glucose lowering effect of the insulin is maximal. The timing of hypoglycemia usually reflects the time-action profile of the administered insulin formulation. As with all insulins, the glucose lowering effect time course of APIDRA may vary in different individuals or at different times in the same individual and depends on many conditions, including the area of injection as well as the injection site blood supply and temperature [see Clinical Pharmacology (12.2)].

Other factors which may increase the risk of hypoglycemia include changes in meal pattern (e.g., macronutrient content or timing of meals), changes in level of physical activity, or changes to concomitant drugs [see Drug Interactions (7)]. Patients with renal or hepatic impairment may be at higher risk of hypoglycemia [see Use in Specific Populations (8.6, 8.7)].

Risk Mitigation Strategies for Hypoglycemia

Patients and caregivers must be educated to recognize and manage hypoglycemia. Self-monitoring of blood glucose plays an essential role in the prevention and management of hypoglycemia. In patients at higher risk for hypoglycemia and patients who have reduced symptomatic awareness of hypoglycemia, increased frequency of blood glucose monitoring is recommended.

5.4 Hypoglycemia Due to Medication Errors

Accidental mix-ups between insulin products have been reported. To avoid medication errors between APIDRA and other insulins, instruct patients to always check the insulin label before each injection [see Adverse Reactions (6.3)].

5.5 Hypokalemia

All insulins, including APIDRA, cause a shift in potassium from the extracellular to intracellular space, possibly leading to hypokalemia. Untreated hypokalemia may cause respiratory paralysis, ventricular arrhythmia, and death. Use caution in patients who may be at risk for hypokalemia (e.g., patients using potassium-lowering medications, patients taking medications sensitive to serum potassium concentrations).

5.6 Hypersensitivity Reactions

Severe, life-threatening, generalized allergy, including anaphylaxis, can occur with insulins, including APIDRA [see Adverse Reactions (6.1)]. If hypersensitivity reactions occur, discontinue APIDRA; treat per standard of care and monitor until symptoms and signs resolve. APIDRA is contraindicated in patients who have had a hypersensitivity reaction to insulin glulisine or any of its excipients.

5.7 Fluid Retention and Heart Failure with Concomitant Use of PPAR-Gamma Agonists

Thiazolidinediones (TZDs), which are peroxisome proliferator-activated receptor (PPAR) gamma agonists, can cause dose-related fluid retention, when used in combination with insulin. Fluid retention may lead to or exacerbate heart failure. Patients treated with insulin, including APIDRA and a PPAR-gamma agonist should be observed for signs and symptoms of heart failure. If heart failure develops, it should be managed according to current standards of care, and discontinuation or dose reduction of the PPAR-gamma agonist must be considered.

5.8 Hyperglycemia and Ketoacidosis Due to Insulin Pump Device Malfunction

Malfunction of the insulin pump or insulin infusion set or insulin degradation can rapidly lead to hyperglycemia and ketoacidosis. Prompt identification and correction of the cause of hyperglycemia or ketosis is necessary. Interim subcutaneous injections with APIDRA may be required. Patients using continuous subcutaneous insulin infusion pump therapy must be trained to administer insulin by injection and have alternate insulin therapy available in case of pump failure [see How Supplied/Storage and Handling (16.2)].

6 ADVERSE REACTIONS

The following adverse reactions are discussed elsewhere:

- Hypoglycemia [see Warnings and Precautions (5.3)]
- Hypoglycemia Due to Medication Errors [see Warnings and Precautions (5.4)]
- Hypokalemia [see Warnings and Precautions (5.5)]
- Hypersensitivity Reactions [see Warnings and Precautions (5.6)]

6.1 Clinical Trials Experience

Because clinical trials are conducted under widely varying designs, the adverse reaction rates reported in one clinical trial may not be easily compared to those rates reported in another clinical trial and may not reflect the rates actually observed in clinical practice.

The data in Table 1 reflect the exposure of 1591 patients with type 1 diabetes to APIDRA or comparators [see Clinical Studies (14.1)]. The type 1 diabetes population had the following characteristics: Mean age was 39.74 years. 54.5 % were male, 95.5% were Caucasian, 1.5% were Black or African American.

The data in Table 2 reflect the exposure of 1766 patients with type 2 diabetes to APIDRA or comparators [see Clinical Studies (14.2)]. The type 2 diabetes population had the following characteristics: Mean age was 59.08 years. 51.2% were male, 88.5% were Caucasian, 7.2% were Black or African American.

The frequencies of adverse drug reactions during APIDRA clinical trials in patients with type 1 diabetes mellitus and type 2 diabetes mellitus are listed in the tables below.

Table 1: Adverse Reactions Occurring ≥5% in Pooled Studies of Adults with Type 1 Diabetes
 | APIDRA, % (n=950) | All Comparators [Insulin lispro, regular human insulin, insulin aspart] , % (n=641)
Nasopharyngitis | 10.6 | 12.9
Hypoglycemia [Only severe symptomatic hypoglycemia] | 6.8 | 6.7
Upper respiratory tract infection | 6.6 | 5.6
Influenza | 4.0 | 5.0

Table 2: Adverse Reactions Occurring ≥5% in Pooled Studies of Adults with Type 2 Diabetes
 | APIDRA, % (n=883) | Regular Human Insulin, % (n=883)
Upper respiratory tract infection | 10.5 | 7.7
Nasopharyngitis | 7.6 | 8.2
Edema peripheral | 7.5 | 7.8
Influenza | 6.2 | 4.2
Arthralgia | 5.9 | 6.3
Hypertension | 3.9 | 5.3

Pediatrics

Table 3 summarizes the adverse reactions occurring with frequency higher than 5% in a clinical study in pediatric patients with type 1 diabetes treated with APIDRA (n=277) or insulin lispro (n=295).

Table 3: Adverse Reactions Occurring ≥5% in Pediatric Patients with Type 1 Diabetes
 | APIDRA, % (n=277) | Insulin Lispro, % (n=295)
Nasopharyngitis | 9.0 | 9.5
Upper respiratory tract infection | 8.3 | 10.8
Headache | 6.9 | 11.2
Hypoglycemic seizure | 6.1 | 4.7

Severe Symptomatic Hypoglycemia

Hypoglycemia was the most commonly observed adverse reaction in patients treated with insulin, including APIDRA. The rates of reported hypoglycemia depend on the definition of hypoglycemia used, diabetes type, insulin dose, intensity of glucose control, background therapies, and other intrinsic and extrinsic patient factors. For these reasons, comparing rates of hypoglycemia in clinical trials for APIDRA with the incidence of hypoglycemia for other products may be misleading and also, may not be representative of hypoglycemia rates that occur in clinical practice. The rates and incidence of severe symptomatic hypoglycemia, defined as hypoglycemia requiring intervention from a third party are presented in Table 4. In the clinical trials, children and adolescents with type 1 diabetes had a higher incidence of severe symptomatic hypoglycemia in the two treatment groups compared to adults with type 1 diabetes (see Table 4) [see Clinical Studies (14)].

Table 4: Severe Symptomatic Hypoglycemia [Severe symptomatic hypoglycemia defined as a hypoglycemic event requiring the assistance of another person that met one of the following criteria: the event was associated with a whole blood referenced blood glucose <36 mg/dL or the event was associated with prompt recovery after oral carbohydrate, intravenous glucose, or glucagon administration.]
 | Type 1 Diabetes Adults 12 weeks with insulin glargine |  |  | Type 1 Diabetes Adults 26 weeks with insulin glargine |  | Type 2 Diabetes Adults 26 weeks with NPH human insulin |  | Type 1 Diabetes Pediatrics 26 weeks
 | APIDRA Pre meal | APIDRA Post meal | Regular Human Insulin | APIDRA | Insulin Lispro | APIDRA | Regular Human Insulin | APIDRA | Insulin Lispro
Events per month per patient | 0.05 | 0.05 | 0.13 | 0.02 | 0.02 | 0.00 | 0.00 | 0.09 | 0.08
Percent of patients (n/total N) | 8.4% (24/286) | 8.4% (25/296) | 10.1% (28/278) | 4.8% (16/339) | 4.0% (13/333) | 1.4% (6/416) | 1.2% (5/420) | 16.2% (45/277) | 19.3% (57/295)

Adverse Reactions with Continuous Subcutaneous Insulin Infusion (CSII)

In a 12-week randomized study in patients with type 1 diabetes (n=59), the rates of catheter occlusions and infusion site reactions were similar for APIDRA and insulin aspart–treated patients (see Table 5).

Table 5: Catheter Occlusions and Infusion Site Reactions
 | APIDRA (n=29) | Insulin Aspart (n=30)
Catheter occlusions/month | 0.08 | 0.15
Infusion site reactions | 10.3% (3/29) | 13.3% (4/30)

Allergic Reactions

Severe, life-threatening, generalized allergy, including anaphylaxis, may occur with any insulin, including APIDRA. Generalized allergy to insulin may cause whole body rash (including pruritus), dyspnea, wheezing, hypotension, tachycardia, or diaphoresis.

In controlled clinical trials up to 12 months duration, potential systemic allergic reactions were reported in 79 of 1833 patients (4.3%) who received APIDRA and 58 of 1524 patients (3.8%) who received the comparator short-acting insulins. During these trials, treatment with APIDRA was permanently discontinued in 1 of 1833 patients due to a potential systemic allergic reaction.

Injection Site Reactions

As with any insulin, patients taking APIDRA may experience redness, swelling, or itching at the site of injection. These minor reactions usually resolve in a few days to a few weeks, but on some occasions may require discontinuation of APIDRA. In some instances, these reactions may be related to factors other than insulin, such as irritants in a skin cleansing agent or poor injection technique.

Insulin Initiation and Intensification of Glucose Control

Intensification or rapid improvement in glucose control has been associated with a transitory, reversible ophthalmologic refraction disorder, worsening of diabetic retinopathy, and acute painful peripheral neuropathy. However, long-term glycemic control decreases the risk of diabetic retinopathy and neuropathy.

Lipodystrophy

Long-term use of insulin, including APIDRA, can cause lipodystrophy at the site of repeated insulin injections or infusion. Lipodystrophy includes lipohypertrophy (thickening of adipose tissue) and lipoatrophy (thinning of adipose tissue) and may affect insulin absorption [see Dosage and Administration (2.2)].

Peripheral Edema

Insulins, including APIDRA, may cause sodium retention and edema, particularly if previously poor metabolic control is improved by intensified insulin therapy.

Weight Gain

Weight gain can occur with insulins, including APIDRA, and has been attributed to the anabolic effects of insulin and the decrease in glucosuria.

6.2 Immunogenicity

As with all therapeutic proteins, there is potential for immunogenicity. The detection of antibody formation is highly dependent on the sensitivity and specificity of the assay. Additionally, the observed incidence of antibody (including neutralizing antibody) positivity in an assay may be influenced by several factors including assay methodology, sample handling, timing of sample collection, concomitant medication, and underlying disease. For these reasons, comparison of the incidence of antibodies to APIDRA in the studies described below with the incidence of antibodies in other studies or to other insulin products may be misleading.

In a study in patients with type 1 diabetes (n=333), the concentrations of insulin antibodies that react with both human insulin and insulin glulisine (cross-reactive insulin antibodies) remained near baseline during the first 6 months of the study in the patients treated with APIDRA. A decrease in antibody concentration was observed during the following 6 months of the study. In a study in patients with type 2 diabetes (n=411), a similar increase in cross-reactive insulin antibody concentration was observed in the patients treated with APIDRA and in the patients treated with human insulin during the first 9 months of the study. Thereafter the concentration of antibodies decreased in the APIDRA patients and remained stable in the human insulin patients. There was no correlation between cross-reactive insulin antibody concentration and changes in HbA1c, insulin doses, or incidence of hypoglycemia. APIDRA did not elicit a significant antibody response in a study of pediatric patients with type 1 diabetes.

6.3 Postmarketing Experience

The following adverse reactions have been identified during postapproval use of APIDRA. Because these reactions are reported voluntarily from a population of uncertain size, it is not always possible to estimate reliably their frequency or establish a causal relationship to drug exposure.

Medication errors have been reported in which other insulins, particularly long-acting insulins, have been accidentally administered instead of APIDRA.

Localized cutaneous amyloidosis at the injection site has occurred. Hyperglycemia has been reported with repeated insulin injections into areas of localized cutaneous amyloidosis; hypoglycemia has been reported with a sudden change to an unaffected injection site.

7 DRUG INTERACTIONS

Table 6: Clinically Significant Drug Interactions with APIDRA
Drugs that May Increase the Risk of Hypoglycemia
Drugs: | Antidiabetic agents, ACE inhibitors, angiotensin II receptor blocking agents, disopyramide, fibrates, fluoxetine, monoamine oxidase inhibitors, pentoxifylline, pramlintide, salicylates, somatostatin analog (e.g., octreotide), and sulfonamide antibiotics.
Intervention: | Dose adjustment and increased frequency of glucose monitoring may be required when APIDRA is coadministered with these drugs.
Drugs that May Decrease the Blood Glucose Lowering Effect of APIDRA
Drugs: | Atypical antipsychotics, corticosteroids, danazol, diuretics, estrogens, glucagon, isoniazid, niacin, phenothiazine derivatives, progestogens (e.g., in oral contraceptives), protease inhibitors, somatropin, sympathomimetic agents (e.g., albuterol, epinephrine, terbutaline), and thyroid hormones.
Intervention: | Dose adjustment and increased frequency of glucose monitoring may be required when APIDRA is coadministered with these drugs.
Drugs that May Increase or Decrease the Blood Glucose Lowering Effect of APIDRA
Drugs: | Alcohol, beta-blockers, clonidine, and lithium salts. Pentamidine may cause hypoglycemia, which may sometimes be followed by hyperglycemia.
Intervention: | Dose adjustment and increased frequency of glucose monitoring may be required when APIDRA is coadministered with these drugs.
Drugs that May Blunt Signs and Symptoms of Hypoglycemia
Drugs: | Beta-blockers, clonidine, guanethidine, and reserpine.
Intervention: | Increased frequency of glucose monitoring may be required when APIDRA is coadministered with these drugs.

8 USE IN SPECIFIC POPULATIONS

8.1 Pregnancy

Risk Summary

Available pharmacovigilance data have not established an association with insulin glulisine use during pregnancy and major birth defects, miscarriage or adverse maternal or fetal outcomes. There are risks to the mother and fetus associated with poorly controlled diabetes in pregnancy (see Clinical Considerations). Animal reproduction studies have been conducted with insulin glulisine in rats and rabbits using regular human insulin as a comparator. Insulin glulisine was given to female rats throughout pregnancy at subcutaneous doses up to 10 units/kg/day (2 times the average human dose, based on body surface area comparison) and to rabbits during organogenesis at subcutaneous doses up to 1.5 units/kg/day (0.5 times the average human dose, based on body surface area comparison). The effects did not differ from those observed with subcutaneous regular human insulin (see Data).

In the U.S. general population, the estimated background risk of major birth defects and miscarriage in clinically recognized pregnancies is 2% to 4% and 15% to 20%, respectively. The estimated background risk of major birth defects is 6% to 10% in women with pre-gestational diabetes with a peri-conceptional HbA1c >7 and has been reported to be as high as 20% to 25% in women with a peri-conceptional HbA1c >10. The estimated background risk of miscarriage for the indicated population is unknown.

Clinical Considerations

Disease-associated maternal and/or embryo-fetal risk

Hypoglycemia and hyperglycemia occur more frequently during pregnancy in patients with pre-gestational diabetes. Poorly controlled diabetes in pregnancy increases the maternal risk for diabetic ketoacidosis, pre-eclampsia, spontaneous abortions, preterm delivery, and delivery complications. Poorly controlled diabetes increases the fetal risk for major birth defects, still birth, and macrosomia-related morbidity.

Data

Animal data

Insulin glulisine was given to pregnant female rabbits during gestation at doses up to 1.5 units/kg/day, resulting in an exposure 0.5 times the average human dose, based on body surface area. Adverse effects on embryo-fetal development, including postimplantation loss and skeletal defects, were observed at dose levels that caused maternal hypoglycemia and mortality.

Insulin glulisine given to pregnant female rats during gestation at doses up to 10 units/kg/day, resulting in an exposure 2 times the average human dose based on body surface area, resulted in maternal toxicity indicative of hypoglycemia but did not adversely affect embryo-fetal development. Postnatal development was not adversely affected following administration of insulin glulisine to pregnant female rats during gestation and throughout lactation at doses up to 8 units/kg/day.

The effects of insulin glulisine did not differ from those observed with regular human insulin used as a comparator in the same studies and administered at the same doses.

8.2 Lactation

Risk Summary

Available data from published literature suggest that human insulin products, including APIDRA, are transferred into human milk. There are no adverse reactions reported in the breastfed infants in the literature. There are no data on the effects of exogenous human insulin products, including APIDRA, on milk production. The developmental and health benefits of breastfeeding should be considered along with the mother's clinical need for APIDRA and any potential adverse effects on the breastfed infant from APIDRA or from the underlying maternal condition.

8.4 Pediatric Use

The safety and effectiveness of APIDRA to improve glycemic control have been established in pediatric patients. Use of APIDRA for this indication is supported by evidence from an active-controlled non-inferiority study in pediatric patients 4 years of age and older with type 1 diabetes mellitus treated with APIDRA (n=271) and from studies in adults with diabetes mellitus [see Clinical Pharmacology (12.3), and Clinical Studies (14)].

In the clinical trials, pediatric patients with type 1 diabetes mellitus had a higher incidence of severe symptomatic hypoglycemia in the two treatment groups compared to adults with type 1 diabetes mellitus [see Adverse Reactions (6.1)].

8.5 Geriatric Use

In clinical trials, APIDRA was administered to 147 patients ≥65 years of age and 27 patients ≥75 years of age. The majority of this small subset of geriatric patients had type 2 diabetes. The change in HbA1c values and hypoglycemia frequencies did not differ by age.

Nevertheless, caution should be exercised when APIDRA is administered to geriatric patients. In geriatric patients with diabetes, the initial dosing, dose increments, and maintenance dosage should be conservative to reduce the risk of hypoglycemia [see Warnings and Precautions (5.3)].

8.6 Renal Impairment

Patients with renal impairment may be at increased risk of hypoglycemia and may require more frequent APIDRA dose adjustment and more frequent blood glucose monitoring [see Warnings and Precautions (5.3) and Clinical Pharmacology (12.3)].

8.7 Hepatic Impairment

Patients with hepatic impairment may be at increased risk of hypoglycemia and may require more frequent APIDRA dose adjustment and more frequent blood glucose monitoring [see Warnings and Precautions (5.3) and Clinical Pharmacology (12.3)].

10 OVERDOSAGE

Excess insulin may cause hypoglycemia and, particularly when given intravenously, hypokalemia. Mild episodes of hypoglycemia usually can be treated with oral glucose. Adjustments in drug dosage, meal patterns, or exercise may be needed. More severe episodes of hypoglycemia with coma, seizure, or neurologic impairment may be treated with a glucagon product for emergency use or concentrated intravenous glucose. Sustained carbohydrate intake and observation may be necessary because hypoglycemia may recur after apparent clinical recovery. Hypokalemia must be corrected appropriately.

11 DESCRIPTION

Insulin glulisine is a rapid-acting human insulin analog used to lower blood glucose. Insulin glulisine is produced by recombinant DNA technology utilizing a non-pathogenic laboratory strain of Escherichia coli (K12). Insulin glulisine differs from human insulin in that the amino acid asparagine at position B3 is replaced by lysine and the lysine in position B29 is replaced by glutamic acid. Insulin glulisine has a molecular weight of 5.823 kDa.

APIDRA (insulin glulisine) injection is a sterile, aqueous, clear, and colorless solution for subcutaneous or intravenous use. Each milliliter of APIDRA contains 100 units insulin glulisine, metacresol (3.15 mg), polysorbate 20 (0.01 mg), sodium chloride (5 mg), tromethamine (6 mg), and water for injection. APIDRA has a pH of approximately 7.3. The pH is adjusted by addition of aqueous solutions of hydrochloric acid and/or sodium hydroxide.

12 CLINICAL PHARMACOLOGY

12.1 Mechanism of Action

Regulation of glucose metabolism is the primary activity of insulins and insulin analogs, including insulin glulisine. Insulins lower blood glucose by stimulating peripheral glucose uptake by skeletal muscle and fat, and by inhibiting hepatic glucose production. Insulins inhibit lipolysis and proteolysis and enhance protein synthesis.

12.2 Pharmacodynamics

Studies in healthy volunteers and patients with diabetes demonstrated that APIDRA has a more rapid onset of action and a shorter duration of activity than regular human insulin when given subcutaneously.

In a study in patients with type 1 diabetes (n=20), the glucose-lowering profiles of APIDRA and regular human insulin were assessed at various times in relation to a standard meal at a dose of 0.15 units/kg (see Figure 1).

The maximum blood glucose excursion (ΔGLUmax; baseline subtracted glucose concentration) for APIDRA injected 2 minutes before a meal was 65 mg/dL compared to 64 mg/dL for regular human insulin injected 30 minutes before a meal (see Figure 1A), and 84 mg/dL for regular human insulin injected 2 minutes before a meal (see Figure 1B). The maximum blood glucose excursion for APIDRA injected 15 minutes after the start of a meal was 85 mg/dL compared to 84 mg/dL for regular human insulin injected 2 minutes before a meal (see Figure 1C).

Figure 1: Serial mean blood glucose collected up to 6 hours following a single dose of APIDRA and regular human insulin. APIDRA given 2 minutes (APIDRA - pre) before the start of a meal compared to regular human insulin given 30 minutes (Regular - 30 min) before start of the meal (see Figure 1A) and compared to regular human insulin (Regular - pre) given 2 minutes before a meal (see Figure 1B). APIDRA given 15 minutes (APIDRA - post) after start of a meal compared to regular human insulin (Regular - pre) given 2 minutes before a meal (see Figure 1C). On the x-axis, zero (0) is the start of a 15-minute meal.

In a randomized, open-label, two-way crossover study, 16 healthy male subjects received an intravenous infusion of APIDRA or regular human insulin with saline diluent at a rate of 0.8 milliunits/kg/min for two hours. Infusion of the same dose of APIDRA or regular human insulin produced equivalent glucose disposal at steady state.

12.3 Pharmacokinetics

Absorption and Bioavailability

Pharmacokinetic profiles in healthy volunteers and patients with diabetes (type 1 or type 2) demonstrated that absorption of insulin glulisine was faster than that of regular human insulin.

In a study in patients with type 1 diabetes (n=20) after subcutaneous administration of 0.15 units/kg, the median time to maximum concentration (Tmax) was 60 minutes (range 40 to 120 minutes) and the peak concentration (Cmax) was 83 microunits/mL (range 40 to 131 microunits/mL) for insulin glulisine compared to a median Tmax of 120 minutes (range 60 to 239 minutes) and a Cmax of 50 microunits/mL (range 35 to 71 microunits/mL) for regular human insulin (see Figure 2).

Figure 2: Pharmacokinetic Profiles of Insulin Glulisine and Regular Human Insulin in Patients with Type 1 Diabetes after a Dose of 0.15 units/kg.

Insulin glulisine and regular human insulin were administered subcutaneously at a dose of 0.2 units/kg in a euglycemic clamp study in patients with type 2 diabetes (n=24) and a body mass index (BMI) between 20 and 36 kg/m^2. The median time to maximum concentration (Tmax) was 100 minutes (range 40 to 120 minutes) and the median peak concentration (Cmax) was 84 microunits/mL (range 53 to 165 microunits/mL) for insulin glulisine compared to a median Tmax of 240 minutes (range 80 to 360 minutes) and a median Cmax of 41 microunits/mL (range 33 to 61 microunits/mL) for regular human insulin (see Figure 3).

Figure 3: Pharmacokinetic Profiles of Insulin Glulisine and Regular Human Insulin in Patients with Type 2 Diabetes after a Subcutaneous Dose of 0.2 units/kg.

When APIDRA was injected subcutaneously into different areas of the body, the time-concentration profiles were similar. The absolute bioavailability of insulin glulisine after subcutaneous administration is approximately 70%, regardless of injection area (abdomen 73%, deltoid 71%, thigh 68%).

In a clinical study in healthy volunteers (n=32) the total insulin glulisine bioavailability was similar after subcutaneous injection of insulin glulisine and NPH insulin (premixed in the syringe) and following separate simultaneous subcutaneous injections. There was 27% attenuation of the maximum concentration (Cmax) of APIDRA after premixing; however, the time to maximum concentration (Tmax) was not affected.

Distribution and Elimination

The distribution and elimination of insulin glulisine and regular human insulin after intravenous administration are similar with volumes of distribution of 13 and 21 L and half-lives of 13 and 17 minutes, respectively. After subcutaneous administration, insulin glulisine is eliminated more rapidly than regular human insulin with an apparent half-life of 42 minutes compared to 86 minutes.

Specific Populations

Pediatric patients

The pharmacokinetic and pharmacodynamic properties of APIDRA and regular human insulin were assessed in a study conducted in pediatric patients 7 to 11 years old (n=10) and 12 to 16 years old (n=10) with type 1 diabetes. The relative differences in pharmacokinetics and pharmacodynamics between APIDRA and regular human insulin in these patients with type 1 diabetes were similar to those in healthy adult subjects and adults with type 1 diabetes.

Race

A study in 24 healthy Caucasians and Japanese subjects compared the pharmacokinetics and pharmacodynamics after subcutaneous injection of insulin glulisine, insulin lispro, and regular human insulin. With subcutaneous injection of insulin glulisine, Japanese subjects had a greater initial exposure (33%) for the ratio of AUC(0–1h) to AUC(0–clamp end) than Caucasians (21%) although the total exposures were similar. There were similar findings with insulin lispro and regular human insulin.

Obesity

Insulin glulisine and regular human insulin were administered subcutaneously at a dose of 0.3 units/kg in a euglycemic clamp study in obese, non-diabetic subjects (n=18) with a body mass index (BMI) between 30 and 40 kg/m^2. The median time to maximum concentration (Tmax) was 85 minutes (range 49 to 150 minutes) and the median peak concentration (Cmax) was 192 microunits/mL (range 98 to 380 microunits/mL) for insulin glulisine compared to a median Tmax of 150 minutes (range 90 to 240 minutes) and a median Cmax of 86 microunits/mL (range 43 to 175 microunits/mL) for regular human insulin.

The more rapid onset of action and shorter duration of activity of APIDRA and insulin lispro compared to regular human insulin were maintained in an obese non-diabetic population (n=18) (see Figure 4).

Figure 4: Glucose Infusion Rates (GIR) in a Euglycemic Clamp Study after Subcutaneous Injection of 0.3 units/kg of APIDRA, Insulin Lispro or Regular Human Insulin in an Obese Population.

Renal impairment

Studies with human insulin have shown increased circulating levels of insulin in patients with renal failure. In a study performed in 24 non-diabetic subjects with normal renal function (ClCr >80 mL/min), moderate renal impairment (30–50 mL/min), and severe renal impairment (<30 mL/min), the subjects with moderate and severe renal impairment had increased exposure to insulin glulisine by 29% to 40% and reduced clearance of insulin glulisine by 20% to 25% compared to subjects with normal renal function [see Use in Specific Populations (8.6)].

Hepatic impairment

The effect of hepatic impairment on the pharmacokinetics and pharmacodynamics of APIDRA has not been studied. Some studies with human insulin have shown increased circulating levels of insulin in patients with liver failure [see Use in Specific Populations (8.7)].

Gender

The effect of gender on the pharmacokinetics and pharmacodynamics of APIDRA has not been studied.

Smoking

The effect of smoking on the pharmacokinetics and pharmacodynamics of APIDRA has not been studied.

13 NONCLINICAL TOXICOLOGY

13.1 Carcinogenesis, Mutagenesis, Impairment of Fertility

Long-term carcinogenicity studies in animals have not been performed. In Sprague Dawley rats, a 12-month study was conducted with insulin glulisine at subcutaneous doses of 2.5, 5, 20 or 50 units/kg administered twice daily, resulting in an exposure 1, 2, 8, and 20 times the average human dose, based on body surface area.

There was a non-dose dependent higher incidence of mammary gland tumors in female rats administered insulin glulisine compared to untreated controls. The incidence of mammary tumors for insulin glulisine and regular human insulin was similar. Insulin glulisine was not mutagenic in the following tests: Ames test, in vitro mammalian chromosome aberration test in V79 Chinese hamster cells, and in vivo mammalian erythrocyte micronucleus test in rats.

In fertility studies in male and female rats at subcutaneous doses up to 10 units/kg/day (2 times the average human dose, based on body surface area comparison), no clear adverse effects on male and female fertility, or general reproductive performance of animals were observed.

14 CLINICAL STUDIES

The safety and efficacy of APIDRA were studied in adult patients with type 1 and type 2 diabetes (n=1833) and in pediatric patients (4 to 17 years) with type 1 diabetes (n=572). The primary efficacy parameter in these trials was glycemic control, assessed using glycated hemoglobin (GHb reported as HbA1c equivalent).

14.1 Type 1 Diabetes-Adults

A 26-week, randomized, open-label, active-controlled, non-inferiority study was conducted in patients with type 1 diabetes to assess the safety and efficacy of APIDRA (n=339) compared to insulin lispro (n=333) when administered subcutaneously within 15 minutes before a meal. Insulin glargine was administered once daily in the evening as the basal insulin. There was a 4-week run-in period with insulin lispro and insulin glargine prior to randomization. Most patients were Caucasian (97%). Fifty-eight percent of the patients were men. The mean age was 39 years (range 18 to 74 years). Glycemic control, the number of daily short-acting insulin injections and the total daily doses of APIDRA and insulin lispro were similar in the two treatment groups (see Table 7).

Table 7: Type 1 Diabetes Mellitus–Adult
Treatment duration Treatment in combination with: | 26 weeks Insulin glargine
 | APIDRA | Insulin Lispro
Glycated hemoglobin (GHb) [GHb reported as HbA1c equivalent] (%) Number of patients | 331 | 322
Baseline mean | 7.6 | 7.6
Adjusted mean change from baseline | -0.1 | -0.1
Treatment difference: APIDRA – Insulin Lispro | 0.0
95% CI for treatment difference | (-0.1; 0.1)
Basal insulin dose (Units/day)
Baseline mean | 24 | 24
Adjusted mean change from baseline | 0 | 2
Short-acting insulin dose (Units/day)
Baseline mean | 30 | 31
Adjusted mean change from baseline | -1 | -1
Mean number of short-acting insulin injections per day | 3 | 3
Body weight (kg)
Baseline mean | 73.9 | 74.1
Mean change from baseline | 0.6 | 0.3

14.2 Type 2 Diabetes-Adults

A 26-week, randomized, open-label, active-controlled, non-inferiority study was conducted in insulin-treated patients with type 2 diabetes to assess the safety and efficacy of APIDRA (n=435) given within 15 minutes before a meal compared to regular human insulin (n=441) administered 30 to 45 minutes prior to a meal. NPH human insulin was given twice a day as the basal insulin. All patients participated in a 4-week run-in period with regular human insulin and NPH human insulin. Eighty-five percent of patients were Caucasian and 11% were Black. The mean age was 58 years (range 26 to 84 years). The average body mass index (BMI) was 34.6 kg/m^2. At randomization, 58% of the patients were taking an oral antidiabetic agent. These patients were instructed to continue use of their oral antidiabetic agent at the same dose throughout the trial. The majority of patients (79%) mixed their short-acting insulin with NPH human insulin immediately prior to injection. The reductions from baseline in GHb were similar between the 2 treatment groups (see Table 8). No differences between APIDRA and regular human insulin groups were seen in the number of daily short-acting insulin injections or basal or short-acting insulin doses (see Table 8).

Table 8: Type 2 Diabetes Mellitus–Adult
Treatment duration Treatment in combination with: | 26 weeks NPH human insulin
 | APIDRA | Regular Human Insulin
Glycated hemoglobin (GHb) [GHb reported as HbA1c equivalent] (%) Number of patients | 404 | 403
Baseline mean | 7.6 | 7.5
Adjusted mean change from baseline | -0.5 | -0.3
Treatment difference: APIDRA – Regular Human Insulin | -0.2
95% CI for treatment difference | (-0.3; -0.1)
Basal insulin dose (Units/day)
Baseline mean | 59 | 57
Adjusted mean change from baseline | 6 | 6
Short-acting insulin dose (Units/day)
Baseline mean | 32 | 31
Adjusted mean change from baseline | 4 | 5
Mean number of short-acting insulin injections per day | 2 | 2
Body weight (kg)
Baseline mean | 100.5 | 99.2
Mean change from baseline | 1.8 | 2.0

14.3 Type 1 Diabetes-Adults: Pre and Postmeal Administration

A 12-week, randomized, open-label, active-controlled, non-inferiority study was conducted in patients with type 1 diabetes to assess the safety and efficacy of APIDRA administered at different times with respect to a meal. APIDRA was administered subcutaneously either within 15 minutes before a meal (n=286) or immediately after a meal (n=296) and regular human insulin (n=278) was administered subcutaneously 30 to 45 minutes prior to a meal. Insulin glargine was administered once daily at bedtime as the basal insulin. There was a 4-week run-in period with regular human insulin and insulin glargine followed by randomization. Most patients were Caucasian (94%). The mean age was 40 years (range 18 to 73 years). Glycemic control (see Table 9) was comparable for the 3 treatment regimens. No changes from baseline between the treatments were seen in the total daily number of short-acting insulin injections (see Table 9).

Table 9: Pre and Postmeal Administration in Type 1 Diabetes Mellitus–Adult
Treatment duration Treatment in combination with: | 12 weeks insulin glargine | 12 weeks insulin glargine | 12 weeks insulin glargine
 | APIDRA pre meal | APIDRA post meal | Regular Human Insulin
Glycated hemoglobin (GHb) [GHb reported as HbA1c equivalent] (%) Number of patients | 268 | 276 | 257
Baseline mean | 7.7 | 7.7 | 7.6
Adjusted mean change from baseline [Adjusted mean change from baseline treatment difference (98.33% CI for treatment difference): APIDRA pre meal vs Regular Human Insulin -0.1 (-0.3; 0.0) APIDRA post meal vs Regular Human Insulin 0.0 (-0.1; 0.2) APIDRA post meal vs pre meal 0.2 (0.0; 0.3)] | -0.3 | -0.1 | -0.1
Basal insulin dose (Units/day)
Baseline mean | 29 | 29 | 28
Adjusted mean change from baseline | 1 | 0 | 1
Short-acting insulin dose (Units/day)
Baseline mean | 29 | 29 | 27
Adjusted mean change from baseline | -1 | -1 | 2
Mean number of short-acting insulin injections per day | 3 | 3 | 3
Body weight (kg)
Baseline mean | 79.2 | 80.3 | 78.9
Mean change from baseline | 0.3 | -0.3 | 0.3

14.4 Type 1 Diabetes-Pediatric Patients

A 26-week, randomized, open-label, active-controlled, non-inferiority study was conducted in children and adolescents older than 4 years of age with type 1 diabetes mellitus to assess the safety and efficacy of APIDRA (n=277) compared to insulin lispro (n=295) when administered subcutaneously within 15 minutes before a meal. Patients also received insulin glargine (administered once daily in the evening) or NPH insulin (administered once in the morning and once in the evening). There was a 4-week run-in period with insulin lispro and insulin glargine or NPH prior to randomization. Most patients were Caucasian (91%). Fifty percent of the patients were male. The mean age was 12.5 years (range 4 to 17 years). Mean BMI was 20.6 kg/m^2. Glycemic control (see Table 10) was comparable for the two treatment regimens.

Table 10: Results from a 26-Week Study in Pediatric Patients with Type 1 Diabetes Mellitus
 | APIDRA | Insulin Lispro
Number of patients | 271 | 291
Basal Insulin | NPH or insulin glargine | NPH or insulin glargine
Glycated hemoglobin (GHb) [GHb reported as HbA1c equivalent] (%)
Baseline mean | 8.2 | 8.2
Adjusted mean change from baseline | 0.1 | 0.2
Treatment Difference: Mean (95% confidence interval) | -0.1 (-0.2, 0.1)
Basal insulin dose (Units/kg/day)
Baseline mean | 0.5 | 0.5
Mean change from baseline | 0.0 | 0.0
Short-acting insulin dose (Units/kg/day)
Baseline mean | 0.5 | 0.5
Mean change from baseline | 0.0 | 0.0
Mean number of short-acting insulin injections per day | 3 | 3
Baseline mean body weight (kg) Mean weight change from baseline (kg) | 51.5 2.2 | 50.8 2.2

14.5 Type 1 Diabetes-Adults: Continuous Subcutaneous Insulin Infusion

A 12-week randomized, active control study (APIDRA versus insulin aspart) conducted in adults with type 1 diabetes (APIDRA n=29, insulin aspart n=30) evaluated the use of APIDRA in an external continuous subcutaneous insulin pump. All patients were Caucasian. The mean age was 46 years (range 21 to 73 years). The mean GHb increased from baseline to endpoint in both treatment groups (from 6.8% to 7.0% for APIDRA; from 7.1% to 7.2% for insulin aspart).

16 HOW SUPPLIED/STORAGE AND HANDLING

16.1 How Supplied

APIDRA injection, 100 units/mL (U-100), is a clear and colorless solution available as:

APIDRA | NDC number | Package size
10 mL multiple-dose vial | 0088-2500-33 | 1 vial per carton
3 mL single-patient-use APIDRA SoloStar prefilled pen | 0088-2502-05 | 5 pens per carton

Pen needles are not included in the packs.

SoloStar is compatible with all pen needles from Becton Dickinson and Company, Ypsomed, and Owen Mumford.

The APIDRA SoloStar prefilled pen dials in 1-unit increments.

16.2 Storage

Dispense in the original sealed carton with the enclosed Instructions for Use. Do not freeze.

Do not use after the expiration date (see carton and container).

Storage conditions are summarized in the following table:

 | Not in-use (unopened) Refrigerated (36°F-46°F [2°C-8°C]). Protect from light | Not in-use (unopened) Room Temperature (up to 77°F [25°C]) | In-use (opened) (See temperature below)
10 mL multiple-dose vial | Until expiration date | 28 days | 28 days [The in-use time for multiple-dose vial is either 28 days at room temperature up to 77°F (25°C) or 48 hours in insulin pump up to 98.6°F (37°C).] , Refrigerated or room temperature
3 mL single-patient-use APIDRA SoloStar prefilled pen | Until expiration date | 28 days | 28 days, Room temperature (Do not refrigerate)

Use in an External Insulin Pump

Change the APIDRA in the pump reservoir at least every 48 hours, or according to the pump user manual, whichever is shorter, or after exposure to temperatures that exceed 98.6°F (37°C).

Intravenous Use

Diluted APIDRA in infusion bags in normal saline solution (0.9% Sodium Chloride Injection, USP) are stable at room temperature for 48 hours [see Dosage and Administration (2.2)].

17 PATIENT COUNSELING INFORMATION

Advise the patient to read the FDA-approved patient labeling (Patient Information and Instructions for Use).

Never Share an APIDRA SoloStar Pen or Syringe or Needle between Patients

Advise patients that they must never share an APIDRA SoloStar pen with another person, even if the needle is changed. Advise patients using APIDRA vials not to reuse or share needles or syringes with another person. Sharing carries a risk for transmission of blood-borne pathogens [see Warnings and Precautions (5.1)].

Hyperglycemia or Hypoglycemia

Inform patients that hypoglycemia is the most common adverse reaction with insulin. Instruct patients on self-management procedures including glucose monitoring, proper injection technique, and management of hypoglycemia and hyperglycemia, especially at initiation of APIDRA therapy. Instruct patients on handling of special situations such as intercurrent conditions (illness, stress, or emotional disturbances), an inadequate or skipped insulin dose, inadvertent administration of an increased insulin dose, inadequate food intake, and skipped meals. Instruct patients on the management of hypoglycemia [see Warnings and Precautions (5.3)].

Inform patients that their ability to concentrate and react may be impaired as a result of hypoglycemia. Advise patients who have frequent hypoglycemia or reduced or absent warning signs of hypoglycemia to use caution when driving or operating machinery.

Advise patients that changes in insulin regimen can predispose to hyperglycemia or hypoglycemia and that changes in insulin regimen should be made under close medical supervision [see Warnings and Precautions (5.2)].

Hypoglycemia due to Medication Errors

Instruct patients to always check the insulin label before each injection to avoid mix-ups between insulin products [see Warnings and Precautions (5.4)].

Hypersensitivity Reactions

Advise patients that hypersensitivity reactions have occurred with APIDRA. Inform patients on the symptoms of hypersensitivity reactions and to seek medical attention if they occur [see Warnings and Precautions (5.6)].

Instructions For Patients Using Continuous Subcutaneous Insulin Pumps

- Train patients in intensive insulin therapy with multiple injections and in the function of their pump and pump accessories.
- Instruct patients to follow healthcare provider recommendations when setting pump basal rates and bolus settings.
- Refer to the continuous subcutaneous infusion pump user manual to see if APIDRA can be used with the pump. See recommended reservoir and infusion sets in the insulin pump user manual.
- Instruct patients to replace APIDRA in the reservoir at least every 48 hours, or according to the pump user manual, whichever is shorter. By following this schedule, patients avoid insulin degradation, infusion set occlusion, and loss of the insulin preservative.
- Instruct patients that infusion sets and infusion set insertion sites should be changed according to the manufacturer's user manual.
- Instruct patients to discard insulin exposed to temperatures higher than 98.6°F (37°C). The temperature of the insulin may exceed ambient temperature when the pump housing, cover, tubing, or sport case is exposed to sunlight or radiant heat.
- Instruct patients to inform healthcare provider and select a new site for infusion if infusion site becomes erythematous, pruritic, or thickened.
- Instruct patients on the risk of rapid hyperglycemia and ketosis due to pump malfunction; infusion set occlusion, leakage, disconnection, or kinking; and degraded insulin. Instruct patients on the risk of hypoglycemia from pump malfunction. If these problems cannot be promptly corrected, instruct patients to resume therapy with subcutaneous insulin injection and contact their healthcare provider [see Warnings and Precautions (5) and How Supplied/Storage and Handling (16.2)].

Manufactured by:
sanofi-aventis U.S. LLC
Morristown, NJ 07960
A SANOFI COMPANY
U.S. License No. 1752

©2025 sanofi-aventis U.S. LLC

Other brands listed are the registered trademarks of their respective owners and are not trademarks of sanofi-aventis U.S. LLC

PATIENT INFORMATION
APIDRA® (uh PEE druh)
(insulin glulisine) injection for subcutaneous use
100 units/mL (U-100)

Do not share your APIDRA SoloStar® pen or syringes with other people, even if the needle has been changed. You may give other people a serious infection, or get a serious infection from them.

What is APIDRA?
APIDRA is a fast (rapid) acting man-made insulin used to control high blood sugar in adults and children with diabetes mellitus.

Who should not use APIDRA?
Do not use APIDRA if you:

- are having an episode of low blood sugar (hypoglycemia).
- have an allergy to insulin glulisine or any of the ingredients in APIDRA. See the end of this Patient Information leaflet for a complete list of ingredients in APIDRA.

What should I tell my healthcare provider before using APIDRA?
Before using APIDRA, tell your healthcare provider about all your medical conditions including if you:

- have liver or kidney problems.
- take other medicines, especially ones called TZDs (thiazolidinediones).
- have heart failure or other heart problems. If you have heart failure, it may get worse while you take TZDs with APIDRA.
- are pregnant, planning to become pregnant, or are breastfeeding. It is not known if APIDRA may harm your unborn baby or breastfeeding baby.

Tell your healthcare provider about all the medicines you take, including prescription and over-the-counter medicines, vitamins, and herbal supplements.
Before you start using APIDRA, talk to your healthcare provider about low blood sugar and how to manage it.

How should I use APIDRA?

- APIDRA comes in a SoloStar single-patient-use prefilled pen or in a vial.
- Read the detailed Instructions for Use that come with your APIDRA.
- Use APIDRA exactly as your healthcare provider tells you to. Your healthcare provider should tell you how much APIDRA to use and when to use it.
- Know the amount of APIDRA you use. Do not change the amount of APIDRA you use unless your healthcare provider tells you to.
- Know the best time for you to take your insulin. This may change if you take a different type of insulin or if the way you give your insulin changes, for example, using an insulin pump instead of giving injections under the skin (subcutaneous injections).
- Check your insulin label each time you give your injection to make sure you have the correct insulin. This is especially important if you also take long-acting insulin.
- Do not reuse needles. Always use a new needle for each injection. Reuse of needles increase your risk of having blocked needles, which may cause you to get the wrong dose of APIDRA. Using a new needle for each injection lowers your risk of getting an infection.
- APIDRA is a rapid-acting insulin. Take APIDRA within 15 minutes before a meal or within 20 minutes after starting a meal.
- APIDRA is injected under the skin (subcutaneously) of your upper arms, thighs, or stomach area (abdomen), or by continuous infusion under the skin (subcutaneously) through an insulin pump into an area of your body recommended in the instructions that come with your insulin pump.
- Change (rotate) injection sites within the area you chose with each dose to reduce your risk of getting lipodystrophy (pits in skin or thickened skin) and localized cutaneous amyloidosis (skin with lumps) at the injection sites:
  - Do not use the exact same spot for each injection.
  - Do not inject where the skin has pits, is thickened, or has lumps.
  - Do not inject where the skin is tender, bruised, scaly, or hard, or into scars or damaged skin.
- Check your blood sugar levels. Ask your healthcare provider what your blood sugar should be and when you should check your blood sugar levels.

Keep APIDRA and all medicines out of the reach of children.

Your dose of APIDRA may need to change because of:

- a change in level of physical activity or exercise, weight gain or loss, increased stress, illness, change in diet, or because of other medicines you take.

What should I avoid while using APIDRA?
While using APIDRA do not:

- drive or operate heavy machinery until you know how APIDRA affects you.
- drink alcohol or use over-the-counter medicines that contain alcohol.

What are the possible side effects of APIDRA?
APIDRA may cause serious side effects that can lead to death, including:

- low blood sugar (hypoglycemia). Signs and symptoms that may indicate low blood sugar include:
  - dizziness or light-headedness, sweating, trouble concentrating or confusion, headache, blurred vision, slurred speech, shakiness, fast heartbeat, anxiety, irritability or mood change, hunger
- severe allergic reaction (whole body reaction). Get medical help right away if you have any of these signs or symptoms of a severe allergic reaction:
  - a rash over your whole body, shortness of breath, trouble breathing, fast pulse, sweating, or feeling faint
- low potassium in your blood (hypokalemia).
- heart failure. Taking certain diabetes pills called TZDs (thiazolidinediones) with APIDRA may cause heart failure in some people. This can happen even if you have never had heart failure or heart problems before. If you already have heart failure it may get worse while you take TZDs with APIDRA. Your healthcare provider should monitor you closely while you are taking TZDs with APIDRA. Tell your healthcare provider if you have any new or worse symptoms of heart failure including:
  - shortness of breath, swelling of your ankles or feet, sudden weight gain
  Treatment with TZDs and APIDRA may need to be changed or stopped by your healthcare provider if you have new or worse heart failure.

Get emergency medical help if you have:

- trouble breathing, shortness of breath, fast heartbeat, swelling of your face, tongue, or throat, sweating, extreme drowsiness, dizziness, confusion.

The most common side effects of APIDRA include:

- low blood sugar (hypoglycemia), weight gain, itching, rash, swelling, allergic reactions including reactions at your injection site, skin thickening or pits at the injection site (lipodystrophy).

These are not all the possible side effects of APIDRA. Call your doctor for medical advice about side effects. You may report side effects to FDA at 1-800-FDA-1088.

General information about the safe and effective use of APIDRA.
Medicines are sometimes prescribed for purposes other than those listed in a Patient Information leaflet. Do not use APIDRA for a condition for which it was not prescribed. Do not give APIDRA to other people, even if they have the same symptoms that you have. It may harm them.
This Patient Information leaflet summarizes the most important information about APIDRA. If you would like more information, talk with your healthcare provider. You can ask your healthcare provider or pharmacist for information about APIDRA that is written for health professionals.

What are the ingredients in APIDRA?

- Active ingredient: insulin glulisine
- Inactive ingredients: metacresol, polysorbate 20, sodium chloride, tromethamine, and water for injection. Hydrochloric acid and sodium hydroxide may be added to adjust the pH.

Manufactured by: sanofi-aventis U.S. LLC, Morristown, NJ 07960, A SANOFI COMPANY. U.S. License No. 1752
For more information, go to www.APIDRA.com or call 1-800-633-1610.

This Patient Information has been approved by the U.S. Food and Drug Administration.

Revised: May 2025

Instructions for Use
APIDRA® 10 mL vial (100 Units/mL)
(insulin glulisine) injection
for subcutaneous use

These Instructions for Use contain information on how to inject APIDRA using the vial. Read these Instructions for Use before you start taking APIDRA and each time you get a new APIDRA vial. There may be new information. This information does not take the place of talking to your healthcare provider about your medical condition or your treatment.

Do not share your APIDRA syringes with other people, even if the needle has been changed. You may give other people a serious infection, or get a serious infection from them.

Supplies needed to give your injection

- an APIDRA 10 mL vial
- a U-100 insulin syringe and needle
- 2 alcohol swabs
- 1 sharps container for throwing away used needles and syringes. See "Disposing of used needles and syringes" at the end of these instructions.

Preparing your APIDRA dose

- Wash your hands with soap and water or clean your hands with alcohol.
- Check the APIDRA label to make sure that you are taking the right type of insulin. This is especially important if you use more than 1 type of insulin.
- Look at the APIDRA in the vial. It should look clear and colorless. Do not use this vial of APIDRA if the solution is colored, or cloudy, or if you see particles in it.
- Do not use APIDRA after the expiration date stamped on the label or 28 days after you first use it.
- Always use a syringe that is marked for U-100 insulin. If you use a syringe other than a U-100 insulin syringe, you may get the wrong dose of insulin.
- Always use a new syringe or needle for each injection to help prevent infections and prevent blocked needles. Do not reuse or share your syringes or needles with other people. You may give other people a serious infection or get a serious infection from them.

Step 1:

If you are using a new vial, remove the protective cap. Do not remove the stopper.

Step 2:

Wipe the rubber stopper with an alcohol swab. You do not have to shake the vial of APIDRA before use.

Step 3:

Draw air into the syringe equal to the insulin dose. Put the needle through the rubber top of the vial and push the plunger to inject the air into the vial.

Step 4:

Leave the syringe in the vial and turn both upside down. Hold the syringe and vial firmly in one hand. Make sure the tip of the needle is in the insulin. With your free hand, pull the plunger to withdraw the correct dose into the syringe.

Step 5:

Before you take the needle out of the vial, check the syringe for air bubbles. If you see bubbles in the syringe, hold the syringe straight up and tap the side of the syringe with your finger a few times to make any air bubbles float to the top. Gently push the air bubbles out with the plunger and draw insulin back into the syringe until you have the correct dose. If you are mixing APIDRA with NPH insulin, check with your healthcare provider on how to mix it the right way.

Step 6:

Remove the needle from the vial. Do not let the needle touch anything. You are now ready to inject.

Giving your APIDRA injection with a syringe

- Inject your insulin exactly as your healthcare provider has shown you.
- APIDRA starts acting fast, so give your injection within 15 minutes before or right after you eat a meal.

Step 7:

- Choose your injection site: APIDRA is injected under the skin (subcutaneously) of your upper arms, thighs, or stomach area (abdomen).
- Change (rotate) your injection sites within the area you choose for each dose to reduce your risk of getting lipodystrophy (pits in the skin or thickened skin) and localized cutaneous amyloidosis (skin with lumps) at the injection sites.
- Do not inject where the skin has pits, is thickened, or has lumps.
- Do not inject where the skin is tender, bruised, scaly or hard, or into scars or damaged skin.

- Wipe the skin with an alcohol swab to clean the injection site. Let the injection site dry before you inject.

Step 8:

- Pinch the skin.
- Insert the needle in the way your healthcare provider showed you.
- Release the skin.
- Slowly push in the plunger of the syringe all the way, making sure you have injected all the insulin.
- Leave the needle in the skin for about 10 seconds.

Step 9:

- Pull the needle straight out of your skin.
- Gently press the injection site for several seconds. Do not rub the area.
- Do not recap the used needle. Recapping the needle can lead to a needle-stick injury.

Giving your APIDRA using an insulin pump

- If you have been prescribed an insulin pump, check the pump manufacturer's user manual to see if APIDRA can be used with the pump.
- APIDRA should be given into an area of your body recommended in the instructions that come with your insulin pump.
- Change (rotate) your injection sites within the area you choose for each insertion to reduce your risk of getting lipodystrophy (pits in skin or thickened skin) and localized cutaneous amyloidosis (skin with lumps) at the injection sites. Do not inject into the exact same spot for each injection. Do not inject where the skin has pits, is thickened, or has lumps. Do not inject where the skin is tender, bruised, scaly or hard, or into scars or damaged skin.
- Call your healthcare provider and choose a new infusion site if the skin at the infusion site becomes red, itchy, or thickened.
- Change the insulin in the reservoir at least every 2 days or according to the pump user manual, whichever is shorter, even if you have not used all of the insulin.
- Do not dilute or mix APIDRA with other insulins in your insulin pump.
- You should be trained on how to give insulin by injection and have an alternative insulin delivery system in case of pump failure.
- When you start using APIDRA by infusion pump, your insulin dose may need to be adjusted. Check with your healthcare provider before making any changes to your insulin dose.
- Your healthcare provider should provide recommendations for appropriate pump basal and meal-time infusion rates. Call your healthcare provider if you have any questions about using the insulin pump.

Disposing of used needles and syringes

- Put your used needles and syringes in a FDA-cleared sharps disposal container right away after use. Do not throw away (dispose of) loose needles and syringes in your household trash.
- If you do not have a FDA-cleared sharps container, you may use a household container that is:
  - made of a heavy-duty plastic,
  - can be closed with a tight-fitting, puncture-resistant lid, without sharps being able to come out,
  - upright and stable during use,
  - leak resistant, and
  - properly labeled to warn of hazardous waste inside the container.
- When your sharps disposal container is almost full, you will need to follow your community guidelines for the right way to dispose of your sharps disposal container. There may be state or local laws about how you should throw away used needles and syringes. For more information about safe sharps disposal, and for specific information about sharps disposal in the state that you live in, go to the FDA's website at: http://www.fda.gov/safesharpsdisposal.
- Do not dispose of your used sharps disposal container in your household trash unless your community guidelines permit this. Do not recycle your used sharps disposal container.

How should I store APIDRA 10 mL vial?

Unopened (not in-use) APIDRA vials

- Store unused APIDRA vials in the refrigerator from 36°F to 46°F (2°C to 8°C).
- Do not freeze APIDRA.
- Keep APIDRA away from direct heat and light.
- If a vial has been frozen or overheated, throw it away.
- Unopened vials can be used until the expiration date on the carton and label if they have been stored in the refrigerator.
- Unopened vials should be thrown away after 28 days if they are stored at room temperature.

After APIDRA vials have been opened (in-use)

- Store in-use (opened) APIDRA vials in a refrigerator from 36°F to 46°F (2°C to 8°C) or at room temperature below 77°F (25°C) for up to 28 days.
- Do not freeze APIDRA.
- Keep APIDRA out of direct heat and light.
- If a vial has been frozen, throw it away.
- The APIDRA vial you are using should be thrown away after 28 days, even if it still has insulin left in it.

APIDRA in an insulin pump

- Throw away APIDRA in the pump reservoir if it has been exposed to temperatures higher than 98.6°F (37°C). This may occur if the pump housing, cover, tubing, or sport case is exposed to sunlight or direct heat.

This Instructions for Use has been approved by the U.S. Food and Drug Administration.

Revised: May 2025

Manufactured by:
sanofi-aventis U.S. LLC
Morristown, NJ 07960
A SANOFI COMPANY

U.S. License No. 1752

©2025 sanofi-aventis U.S. LLC

INSTRUCTIONS FOR USE

APIDRA® SoloStar®
(insulin glulisine) injection
for subcutaneous use
3 mL single-patient-use PREFILLED PEN: (100 units/mL, U-100)

Read these Instructions for Use before you start taking the APIDRA Solostar pen and each time you get a new APIDRA SoloStar pen. There may be new information. This information does not take the place of talking to your healthcare provider about your medical condition or your treatment.

Do not share your APIDRA SoloStar pen with other people, even if the needle has been changed. You may give other people a serious infection or get a serious infection from them.

People who are blind or have vision problems should not use APIDRA SoloStar prefilled pen without help from a person trained to use APIDRA SoloStar prefilled pen.

APIDRA SoloStar is a disposable prefilled pen used to inject APIDRA. Each APIDRA SoloStar has 300 units of insulin which can be used for many doses. You can select a dose from 1 to 80 units in steps of 1 unit. The pen plunger moves with each dose. The plunger will only move to the end of the cartridge when 300 units of insulin have been given.

Important information You Need to Know Before Injecting APIDRA

- Do not use your pen if it is damaged or if you are not sure that it is working properly.
- Do not use a syringe to remove insulin from your pen.
- Do not reuse needles. If you do, you might get the wrong dose of APIDRA and/or increase the chance of getting an infection.
- Always perform a safety test before each injection (see Step 3).
- Always carry a spare pen and spare needles in case they got lost or stop working.
- Change (rotate) your injection sites within the area you choose for each dose (see "Places to inject").

Learn to inject

- Talk with your healthcare provider about how to inject before using your pen.
- Ask for help if you have problems handling the pen, for example if you have problems with your sight.
- Read all of these instructions before using your pen. If you do not follow all of these instructions, you may get too much or too little insulin.

Need help?

If you have any questions about APIDRA SoloStar or about diabetes, ask your healthcare provider, go to www.apidra.com, or call sanofi-aventis U.S. at 1-800-633-1610.

Extra items you will need:

- a new sterile needle (see Step 2).
- an alcohol swab.
- a puncture-resistant container for used needles and pens. (See "Throwing your pen away".)

Places to inject

- Inject your insulin exactly as your healthcare provider has shown you.
- Inject your insulin under the skin (subcutaneously) of your upper legs (thighs), upper arms, or stomach area (abdomen).
- Change (rotate) your injection sites within the area you choose for each dose to reduce your risk of getting lipodystrophy (pits in skin or thickened skin) and localized cutaneous amyloidosis (skin with lumps) at the injection sites.
- Do not inject where the skin has pits, is thickened, or has lumps.
- Do not inject where the skin is tender, bruised, scaly or hard, or into scars or damaged skin.

Get to know your pen

Step 1. Check your pen

Take a new pen out of the refrigerator at least 1 hour before you inject. Cold insulin is more painful to inject.

1A Check the name and expiration date on the label of your pen.

- Make sure you have the correct insulin.
  - Do not use your pen after the expiration date.

1B Pull off the pen cap.

1C Check that the insulin is clear.

- Do not use the pen if the insulin looks cloudy, colored or contains particles.

1D Wipe the rubber seal with an alcohol swab.

If you have other injector pens:

- Making sure you have the correct medicine is especially important if you have other injector pens.

Step 2. Attach a new needle

- Do not reuse needles. Always use a new sterile needle for each injection. This helps stop blocked needles, contamination, and infection.
- APIDRA SoloStar may be used with pen needles from Becton Dickinson and Company, Ypsomed, and Owen Mumford. Contact your healthcare provider for further information.

2A Take a new needle and peel off the protective seal.

2B Keep the needle straight and screw it onto the pen until fixed. Do not over-tighten.

2C Pull off the outer needle cap. Keep this for later.

2D Pull off the inner needle cap and throw away.

Handling needles

- Take care when handling needles to prevent needle-stick injury and cross-infection.

Step 3. Do a Safety Test

Always do a safety test before each injection to:

- Check your pen and the needle to make sure they are working properly.
- Make sure that you get the correct insulin dose.

3A Select 2 units by turning the dose selector until the dose pointer is at the 2 mark.

3B Press the injection button all the way in.

- When insulin comes out of the needle tip, your pen is working correctly

If no insulin appears:

- You may need to repeat this step up to 3 times before seeing insulin.
- If still no insulin comes out after the third time, the needle may be blocked. If this happens:
  - change the needle (see Step 6 and Step 2),
  - then repeat the safety test (Step 3).
- Do not use your pen if there is still no insulin coming out of the needle tip. Use a new pen.
- Do not use a syringe to remove insulin from your pen.

If you see air bubbles:

- You may see air bubbles in the insulin. This is normal, they will not harm you.

Step 4. Select the Dose

- Do not select a dose or press the injection button without a needle attached. This may damage your pen.

4A Make sure a needle is attached and the dose is set to "0."

4B Turn the dose selector until the dose pointer lines up with your dose.

- If you turn past your dose, you can turn back down.
- If there are not enough units left in your pen for your dose, the dose selector will stop at the number of units left.
- If you cannot select your full prescribed dose, use a new pen or inject the remaining units and use a new pen to complete your dose.

How to read the dose window

Even numbers are shown in line with dose pointer.

20 units selected

Odd numbers are shown as a line between even numbers.

21 units selected

Units of insulin in your pen:

- Your pen contains a total of 300 units of insulin. You can select doses from 1 to 80 units in steps of 1 unit. Each pen contains more than 1 dose.
- You can see roughly how many units of insulin are left by looking at where the plunger is on the insulin scale.

Step 5. Inject your dose

If you find it hard to press the injection button in, do not force it as this may break your pen. See the section below for help.

5A Choose a place to inject as shown in the picture above (Places to inject).

5B Push the needle into your skin as shown by your healthcare provider.

Do not touch the injection button yet.

5C Place your thumb on the injection button. Then press all the way in and hold.

- Do not press at an angle. Your thumb could block the dose selector from turning.

5D Keep the injection button held in and when you see "0" in the dose window, slowly count to 10.

- This will make sure you get your full dose.

5E After holding and slowly counting to 10, release the injection button. Then remove the needle from your skin.

If you find it hard to press the button in:

- Change the needle (see Step 6 and Step 2) then do a safety test (see Step 3).
- If you still find it hard to press in, get a new pen.
- Do not use a syringe to remove insulin from your pen.

Step 6. Remove the Needle

- Take care when handling needles to prevent needle-stick injury and cross-infection.
- Do not put the inner needle cap back on.

6A Grip the widest part of the outer needle cap. Keep the needle straight and guide it into the outer needle cap. Then push firmly on.

- The needle can puncture the cap if it is recapped at an angle.

6B Grip and squeeze the widest part of the outer needle cap. Turn your pen several times with your other hand to remove the needle.

- Try again if the needle does not come off the first time.

6C Throw away the used needle in a puncture-resistant container (see "Throwing your pen away" at the end of this Instructions for Use).

6D Put your pen cap back on.

- Do not put the pen back in the refrigerator.

How to store your pen

Before first use

- Keep new pens in the refrigerator between 36°F to 46°F (2°C to 8°C).
- Do not freeze. Do not use APIDRA if it has been frozen.

After first use

- Keep your pen at room temperature up to 77ºF (25ºC).
- Keep your pen away from heat or light.
- Store your pen with the pen cap on.
- Do not put your pen back in the refrigerator.
- Do not store your pen with the needle attached.
- Keep out of the reach of children.
- Only use your pen for up to 28 days after its first use. Throw away the APIDRA SoloStar pen you are using after 28 days, even if it still has insulin left in it.

How to care for your pen

Handle your pen with care

- Do not drop your pen or knock it against hard surfaces.
- If you think that your pen may be damaged, do not try to fix it. Use a new one.

Protect your pen from dust and dirt

- You can clean the outside of your pen by wiping it with a damp cloth (water only). Do not soak, wash or lubricate your pen. This may damage it.

Throwing your pen away

- The used APIDRA SoloStar pen may be thrown away in your household trash after you have removed the needle.
- Put the used needle in a FDA-cleared sharps disposal container right away after use. Do not throw away (dispose of) loose needles and syringes in your household trash.
- If you do not have a FDA-cleared sharps disposal container, you may use a household container that is:
  - made of a heavy-duty plastic,
  - can be closed with a tight-fitting, puncture-resistant lid, without sharps being able to come out,
  - upright and stable during use,
  - leak-resistant, and
  - properly labeled to warn of hazardous waste inside the container.
- When your sharps disposal container is almost full, you will need to follow your community guidelines for the right way to dispose of your sharps disposal container. There may be state or local laws about how you should throw away used needles and syringes. For more information about safe sharps disposal, and for specific information about sharps disposal in the state that you live in, go to the FDA's website at: https://fda.gov/safesharpsdisposal.
- Do not dispose of your used sharps disposal container in your household trash unless your community guidelines permit this. Do not recycle your used sharps disposal container.

This Instructions for Use has been approved by the U.S. Food and Drug Administration.

Revised: May 2025

Manufactured by:
sanofi-aventis U.S. LLC
Morristown, NJ 07960
A SANOFI COMPANY
U.S. License No. 1752

©2025 sanofi-aventis U.S. LLC

PRINCIPAL DISPLAY PANEL - 10 mL Vial Carton

NDC 0088-2500-33
Rx only

Apidra®
(insulin glulisine)
injection

100 units/mL
(U-100)

For subcutaneous use

For intravenous infusion
after further dilution
ONLY under direct
medical supervision

Use only if solution is
clear and colorless
with no particles visible

One 10 mL
multiple-dose vial

sanofi

PRINCIPAL DISPLAY PANEL - 3 mL Pen Carton

NDC 0088-2502-05
Rx only

Apidra® SoloStar®
(insulin glulisine) injection

For Single Patient Use Only

100 units/mL (U-100)
For subcutaneous use

Five 3 mL prefilled pens – Dispense in this sealed carton
Solution for injection in a disposable insulin delivery device
Use only if solution is clear and colorless with no particles visible
Use within 28 days after initial use
*Needles not included (see back panel)

sanofi